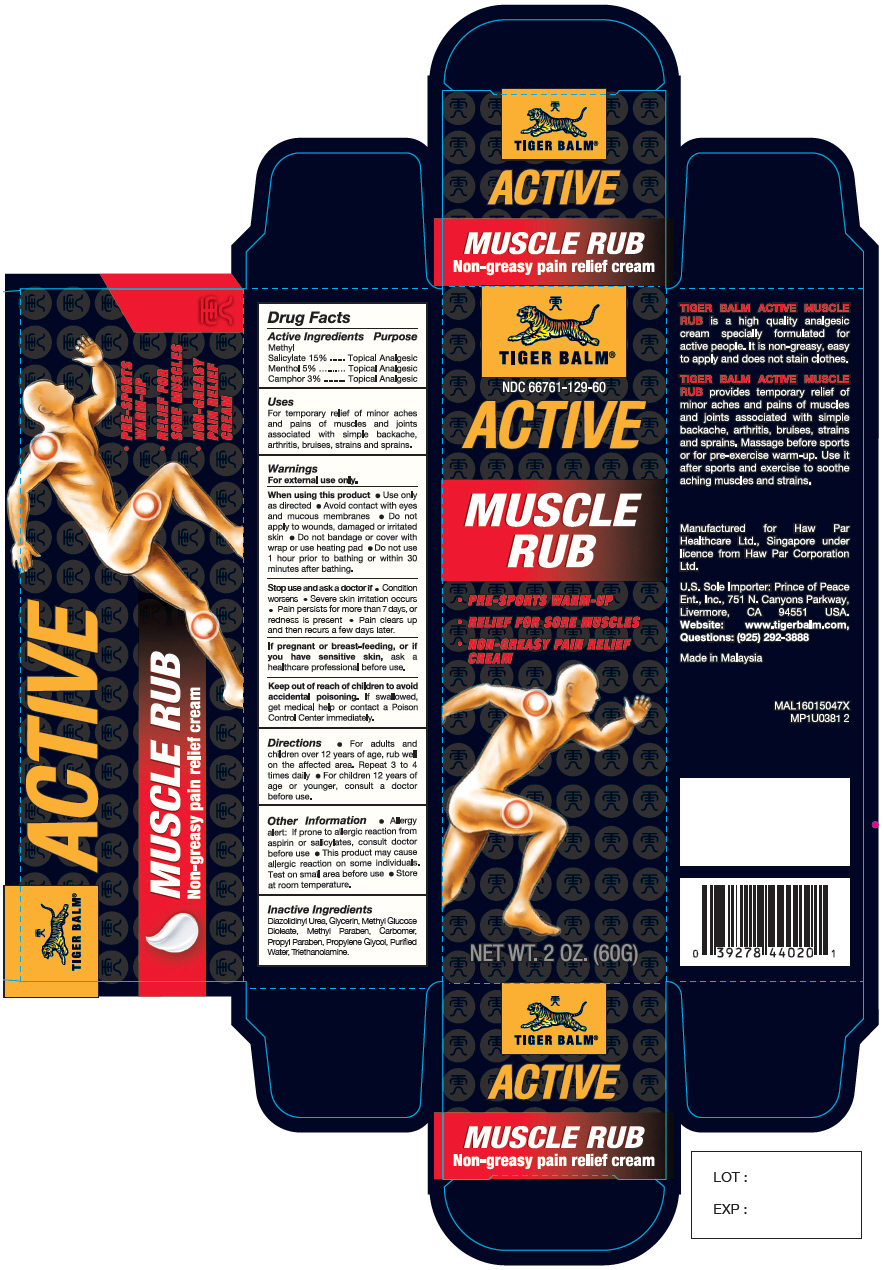 DRUG LABEL: Tiger Balm
NDC: 66761-129 | Form: CREAM
Manufacturer: Haw Par Healthcare Ltd.
Category: otc | Type: HUMAN OTC DRUG LABEL
Date: 20260209

ACTIVE INGREDIENTS: METHYL SALICYLATE 150 mg/1 g; MENTHOL, UNSPECIFIED FORM 50 mg/1 g; CAMPHOR (SYNTHETIC) 30 mg/1 g
INACTIVE INGREDIENTS: CARBOMER HOMOPOLYMER, UNSPECIFIED TYPE; DIAZOLIDINYL UREA; GLYCERIN; METHYL GLUCOSE DIOLEATE; METHYLPARABEN; PROPYLPARABEN; PROPYLENE GLYCOL; WATER; TROLAMINE

Tiger Balm®
Active Muscle Rub

Drug Facts

ACTIVE INGREDIENT

Active Ingredients | Purpose
Methyl Salicylate 15% | Topical Analgesic
Menthol 5% | Topical Analgesic
Camphor 3% | Topical Analgesic

Uses

For temporary relief of minor aches and pains of muscles and joints associated with simple backache, arthritis, bruises, strains and sprains.

Warnings

For external use only.

When using this product

- Use only as directed
- Avoid contact with eyes and mucous membranes
- Do not apply to wounds, damaged or irritated skin
- Do not bandage or cover with wrap or use heating pad
- Do not use 1 hour prior to bathing or within 30 minutes after bathing.

Stop use and ask a doctor if

- Condition worsens
- Severe skin irritation occurs
- Pain persists for more than 7 days
- Pain clears up and then recurs a few days later.

PREGNANCY OR BREAST FEEDING

If pregnant or breast-feeding, or if you have sensitive skin,ask a healthcare professional before use.

Keep out of reach of children.If swallowed, get medical help or contact a Poison Control Center immediately.

Directions

- For adults and children over 12 years of age, rub well on the affected area. Repeat 3 to 4 times daily
- For children 12 years of age or younger, consult a doctor before use.

Other Information

- Allergy alert: If prone to allergic reaction from aspirin or salicylates, consult doctor before use
- This product may cause allergic reaction on some individuals. Test on small area before use
- Store at room temperature.

Inactive Ingredients

Diazolidinyl Urea, Glycerin, Methyl Glucose Dioleate, Methyl Paraben, Carbomer, Propyl Paraben, Propylene Glycol, Purified Water, Triethanolamine.

Questions

(925) 292-3888

PRINCIPAL DISPLAY PANEL - 60G Tube Box

TIGER BALM®

NDC 66761-129-60

ACTIVE

MUSCLE
RUB

- PRE-SPORTS WARM-UP
- RELIEF FOR SORE MUSCLES
- NON-GREASY PAIN RELIEF
  CREAM

NET WT. 2 OZ. (60G)